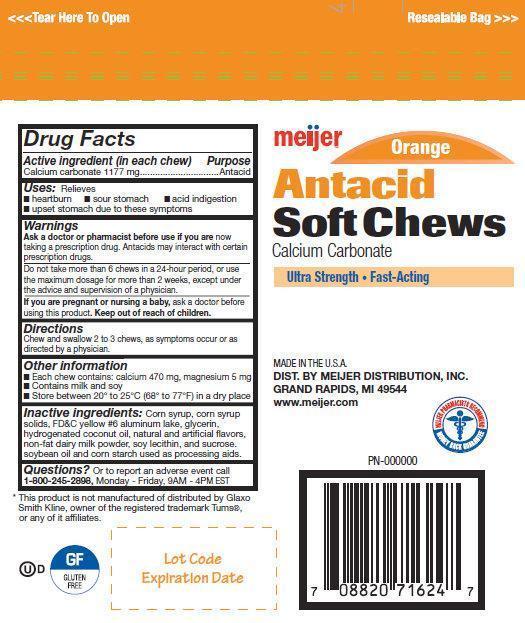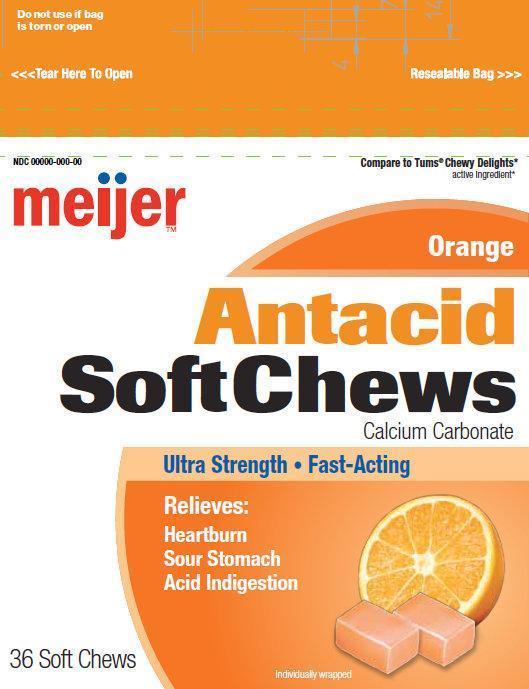 DRUG LABEL: Meijer Softchews
NDC: 41250-079 | Form: BAR, CHEWABLE
Manufacturer: MEIJER DISTRIBUTION, INC
Category: otc | Type: HUMAN OTC DRUG LABEL
Date: 20140604

ACTIVE INGREDIENTS: CALCIUM CARBONATE 1177 mg/1 1
INACTIVE INGREDIENTS: STARCH, CORN; CORN SYRUP; FD&C YELLOW NO. 6; GLYCERIN; HYDROGENATED COCONUT OIL; COW MILK; POTASSIUM SORBATE; LECITHIN, SOYBEAN; SUCROSE

Meijer Orange Softchews

Active ingredient (in each chew)

Calcium carbonate 1177 mg

Purpose

Antacid

Warnings

Ask a doctor or pharmacist before use if you are

now taking a prescription drug. Antacids may interact with certain prescription drugs.

WHEN USING

Do not take more than 6 chews in 24 hours, or use the maximum dosage for more than 2 weeks, except under the advice and supervision of a physician.

If you are pregnant or nursing a baby,

ask a doctor before using this product.

Directions

Chew and swallow 2 to 3 chews, as symptoms occur or as directed by a physician

Other information

- Each chew contains: calcium 470 mg, magnesium 5 mg
- Contains milk and soy
- Store between 20° to 25°C (68° to 77°F) in a dry place

Inactive ingredients

Corn syrup, corn syrup, solids, FD&C yellow #6 aluminum lake, glycerin, hydrogenated coconut oil, natural and articial -avors, non-fat dairy milk powder, soy lecithin, and sucrose. soybean oil and corn starch used as processing aids.

Questions?

Or to report an adverse event call 1-800-245-2898, Monday - Friday, 9AM - 4PM EST

Meijer Orange Antacid Softchews, 36 Count (41250-079-00)

meijer Compare to Tums Chewy Delights

active Ingredients

Orange

Antacid

SoftChews

Calcium Carbonate

Ultra Strength • Fast-Acting

Relieves:

Heartburn

Sour Stomach

Acid Indigestion

36 Soft Chews

This product is not manufactured of distributed by Glaxo

Smith Kline, owner of the registered trademark Tums

®, or any of it afliates.

MADE IN THE U.S.A.

DIST. BY MEIJER DISTRIBUTION, INC.

GRAND RAPIDS, MI 49544

www.meijer.com